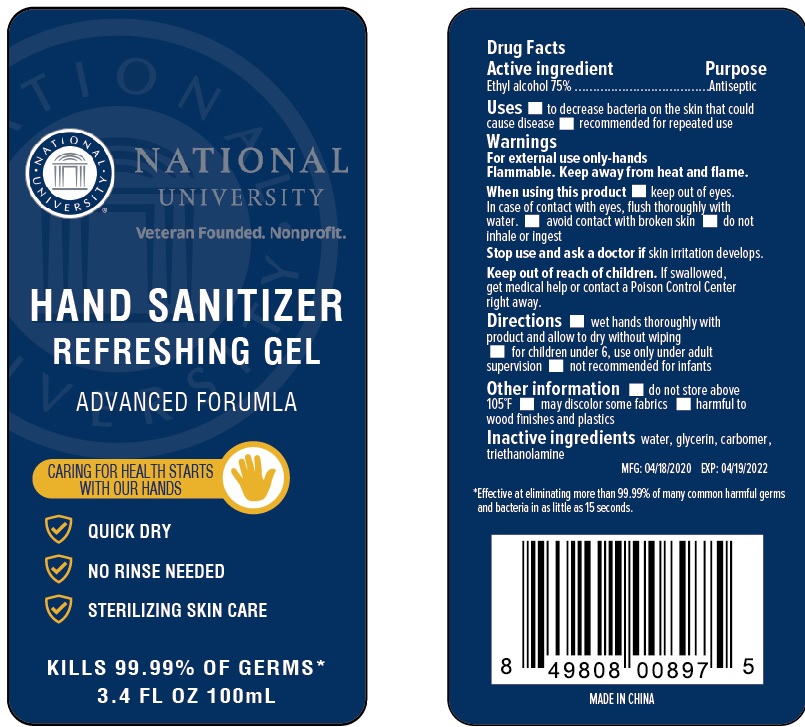 DRUG LABEL: Archstone Hand Sanitizer
NDC: 75531-016 | Form: GEL
Manufacturer: Zhejiang Ounuo Cosmetics Co., Ltd.
Category: otc | Type: HUMAN OTC DRUG LABEL
Date: 20200722

ACTIVE INGREDIENTS: alcohol 75 mL/100 mL
INACTIVE INGREDIENTS: WATER; PROPYLENE GLYCOL; GLYCERIN; CARBOMER COPOLYMER TYPE A; AMINOMETHYLPROPANOL

Drug facts

ACTIVE INGREDIENT

Alcohol .................... 75%

PURPOSE

Antiseptic

KEEP OUT OF REACH OF CHILDREN

If swallowed, get medical help or contact a Poison Control Center right away.

INDICATIONS AND USAGE

- to decrease bacteria on the skin that could cause disease
- recommended for repeated use.

WARNINGS

For external use only: hands
Flammable. Keep away from heat or flame.

When using this products

- keep out of eyes. In case of contact with eyes, flush thoroughly with water
- avoid contact with broken skin
- do not inhale or ingest

Stop using and ask a doctor if irritation develops.

Other information

- do not store above 105℉
- may discolor some fabrics
- harmful to wood finishes and plastics

DOSAGE AND ADMINISTRATION

- Wet hands thoroughly with product and allow to dry without wiping.
- for children under 6, use only under adult supervision
- not recommended for infants

INACTIVE INGREDIENT

Water (aqua), propylene glycol, Glycerin, acrylates/c10-30 alkyl acrylate crosspolymer, aminomethyl Propanol, fragrance (parfum).